DRUG LABEL: TIOCONAZOLE
NDC: 63094-0426 | Form: OINTMENT
Manufacturer: DPT Laboratories, Ltd. 
Category: otc | Type: HUMAN OTC DRUG LABEL
Date: 20090831

ACTIVE INGREDIENTS: TIOCONAZOLE 65 mg/1 g
INACTIVE INGREDIENTS: BUTYLATED HYDROXYANISOLE; MAGNESIUM ALUMINUM SILICATE; PETROLATUM

Active ingredient
(in each applicator)
Tioconazole 300 mg (6.5%)
Purpose
vaginal antifungal

Use

- treats vaginal yeast infections

Warnings

For vaginal use only

Do not use if you have never had a vaginal yeast infection diagnosed by a doctor

Ask a doctor before use if you have

- vaginal itching and discomfort for the first time
- lower abdominal, back or shoulder pain, fever, chills, nausea, vomiting, or foul-smelling vaginal discharge. You may have a more serious condition.
- vaginal yeast infections often (such as once a month or 3 in 6 months). You could be pregnant or have a serious underlying medical cause for your symptoms, including diabetes or a weakened immune system.
- been exposed to human immunodeficiency virus (HIV) that causes AIDS

When using this product

- do not use tampons, douches, spermicides, or other vaginal products. Condoms and diaphragms may be damaged and fail to prevent pregnancy or sexually transmitted disease (STDs).
- do not have vaginal intercourse
- mild increase in vaginal burning, itching or irritation may occur

Stop use and ask a doctor if

- symptoms do not get better after 3 days
- symptoms last more than 7 days
- you get a rash or hives, abdominal pain, fever, chills, nausea, vomiting, or foul-smelling vaginal discharge

PREGNANCY OR BREAST FEEDING

If pregnant or breast-feeding, ask a health professional before use.

Keep out of reach of children. If swallowed, get medical help or contact a Poison Control Center right away.

Directions

- before using this product read the enclosed brochure and instructions on foil packet for complete directions and information
- adults and children 12 years and over: 1.Open the foil packet just before use and remove purple cap. 2.Insert entire contents of applicator into the vagina at bedtime. Throw applicator away after use.
- children under 12 years of age: ask a doctor

Other information

- this product is a 1-dose treatment, most women do not experience complete relief of their symptoms in just one day. Most women experience some relief within one day and complete relief of symptoms within 7 days.
- if you have questions about vaginal yeast infections, consult your doctor
- store at 20 - 25°C (68 - 77°F)
- see end flap of carton for lot number and expiration date

Inactive ingredients

butylated hydroxyanisole, magnesium aluminum silicate, white petrolatum

Do not use if sealed foil packet torn, open, or incompletely sealed.
1-DOSE TREATMENT
TIOCONAZOLE OINTMENT 6.5%
VAGINAL ANTIFUNGAL
DIRECTIONS FOR USE

- Tear open foil packet just before using. It is best to use at bedtime.
- Remove applicator and plunger from packet. Applicator is prefilled with vaginal ointment.
- While firmly holding the purple-capped end of the applicator, push the tip of the plunger into the base of applicator.

REMOVE PURPLE CAP from top of applicator with a pull-twist action.
Insert the applicator

- Lie on your back with your knees bent. Gently insert applicator into the vagina as far as it will go comfortably.
- Push the plunger into the applicator until it will go no farther. Withdraw the applicator and plunger and dispose of it in the wastebasket. Do not flush.
- DO NOT USE TAMPONS while using this medicine. Use sanitary napkins instead.

PLEASE READ EDUCATIONAL BROCHURE FOR ADDITIONAL INFORMATION.
4260000 P6
DISTRIBUTED BY
PERRIGO
ALLEGAN, MI 48010 U.S.A.